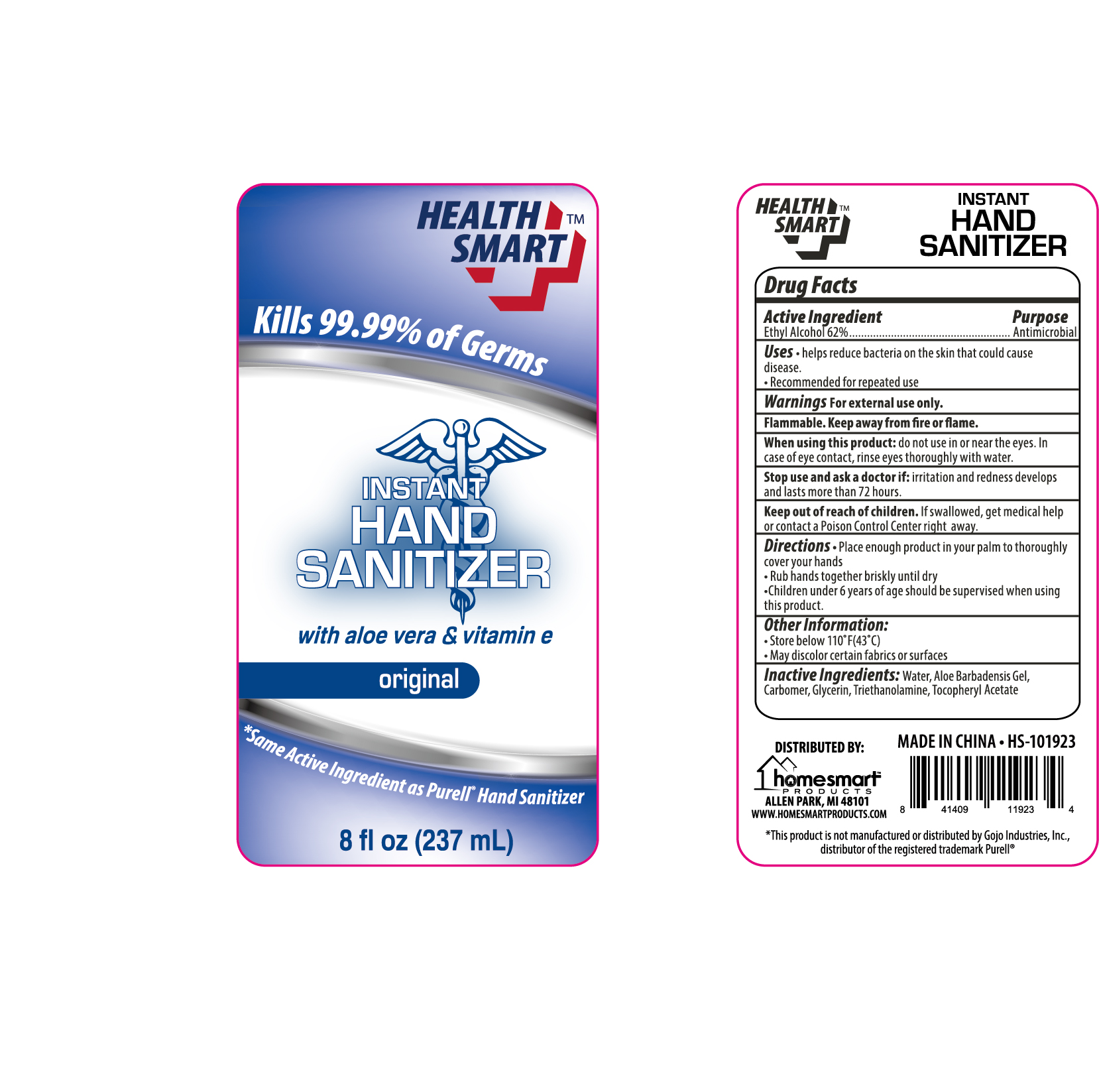 DRUG LABEL: Health Smart Instant Hand Sanitizer
NDC: 75112-003 | Form: SOLUTION
Manufacturer: Zhejiang Shenying Technology Co., Ltd. Jiaojiang Branch
Category: otc | Type: HUMAN OTC DRUG LABEL
Date: 20200522

ACTIVE INGREDIENTS: ALCOHOL 62 mL/100 mL
INACTIVE INGREDIENTS: GLYCERIN; WATER; CARBOMER 934; ALPHA-TOCOPHEROL ACETATE; TROLAMINE; ALOE VERA WHOLE

NA

Active Ingredient(s)

Ethyl Alcohol 62%

Purpose

Antimicrobial

Use

Helps reducing bacteria that potentially can cause disease

Recommended for repeated use

Warnings

For external use only

Flammable. Keep away from fire or flame

When using this product do not use in or near eyes. In case of eye contact, flush eyes thoroughly with water.

Stop use and ask a doctor if irritation or redness develops and lasts for more than 72 hours

Keep out of reach of children. If swallowed, get medical help or contact a Poison Control Center right away.

Directions

Place enough product in your palm to thoroughly cover your hands.

Rub hands together briskly untill dry

Children under six years of age should be supervised when using this product

Other information

Store below 110F (43C)

May discolor certain fabrics or surfaces

Inactive ingredients

Water, aloe barbadensis gel, carbomer, fragrance, glycerin, triethanolamine, tocopheryl acetate